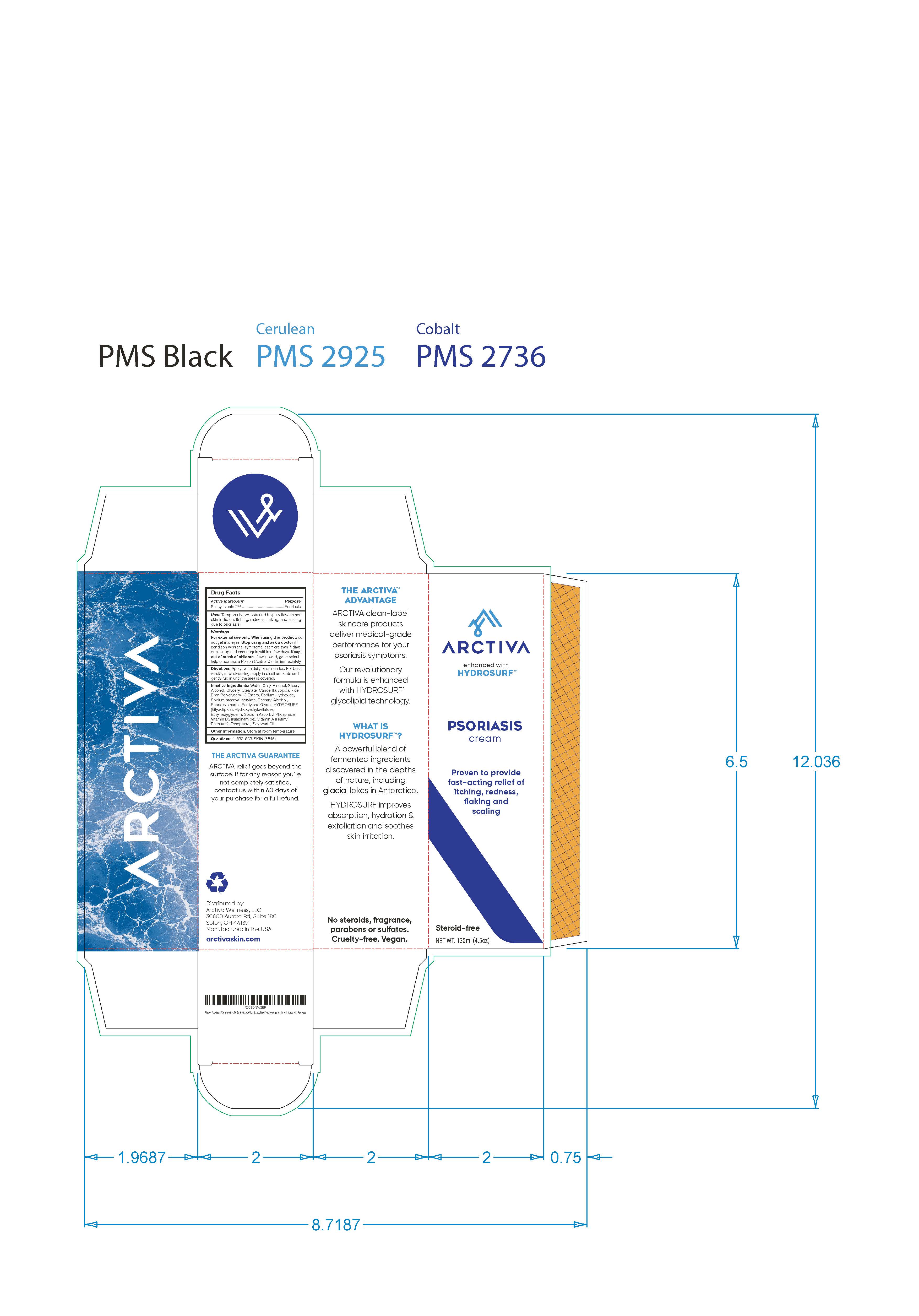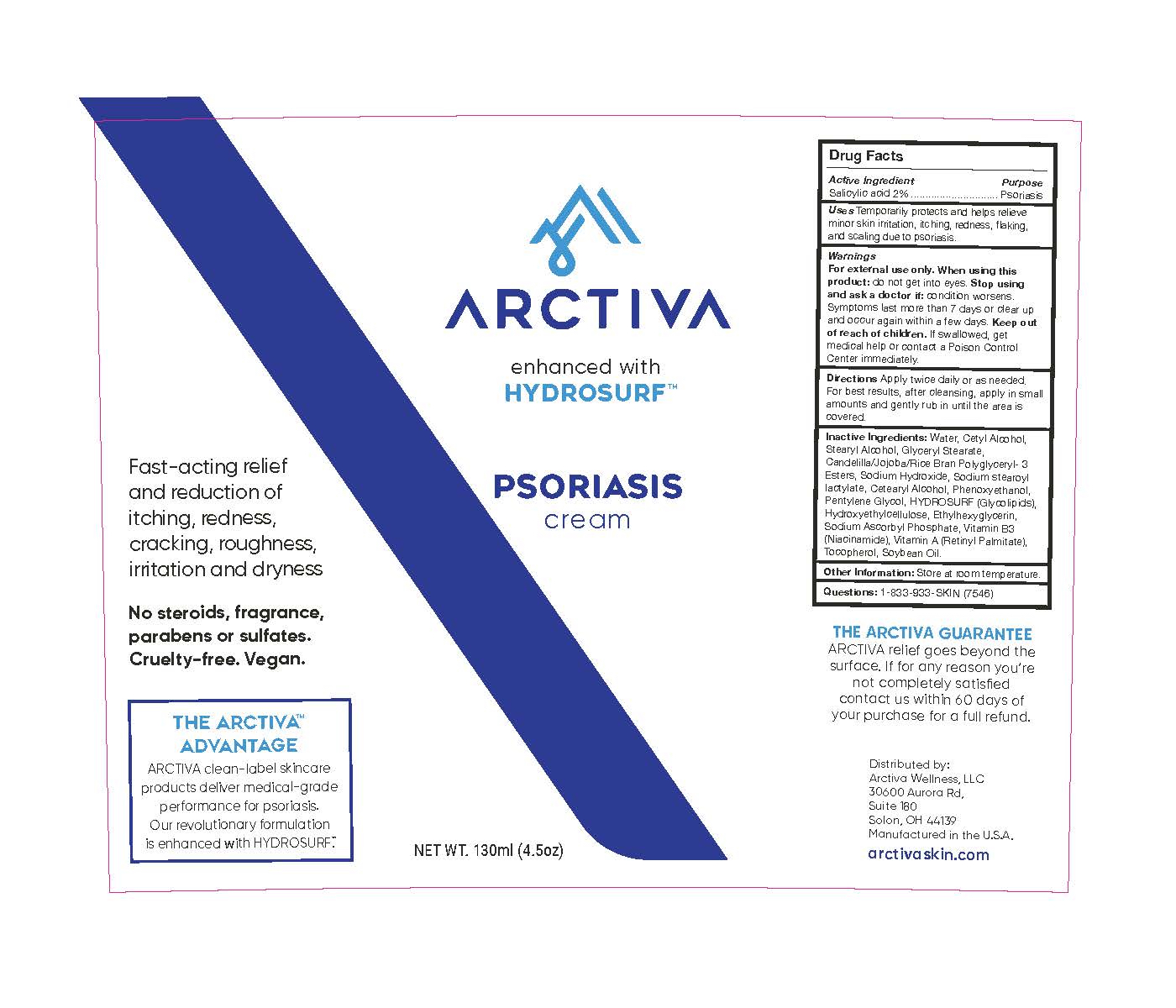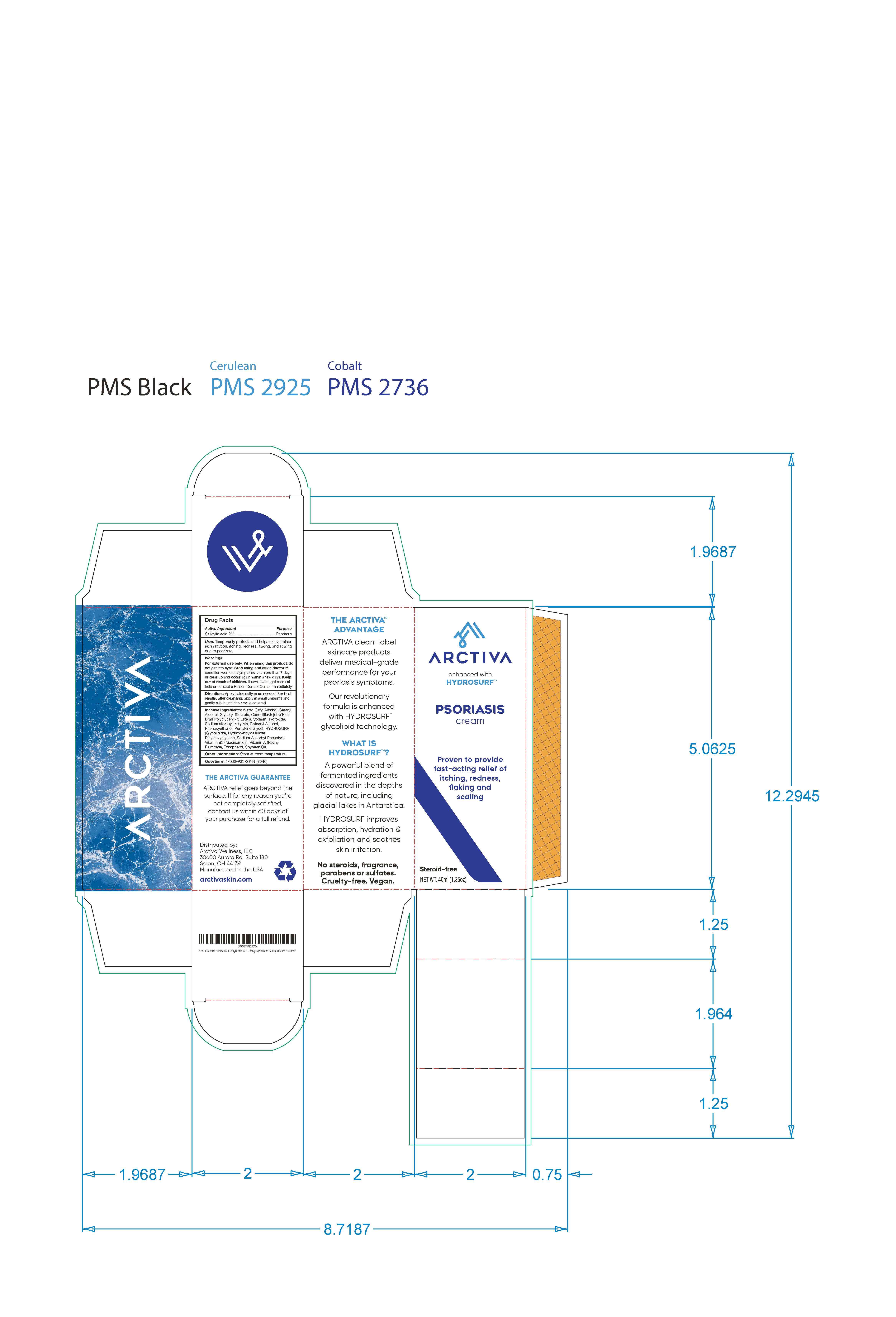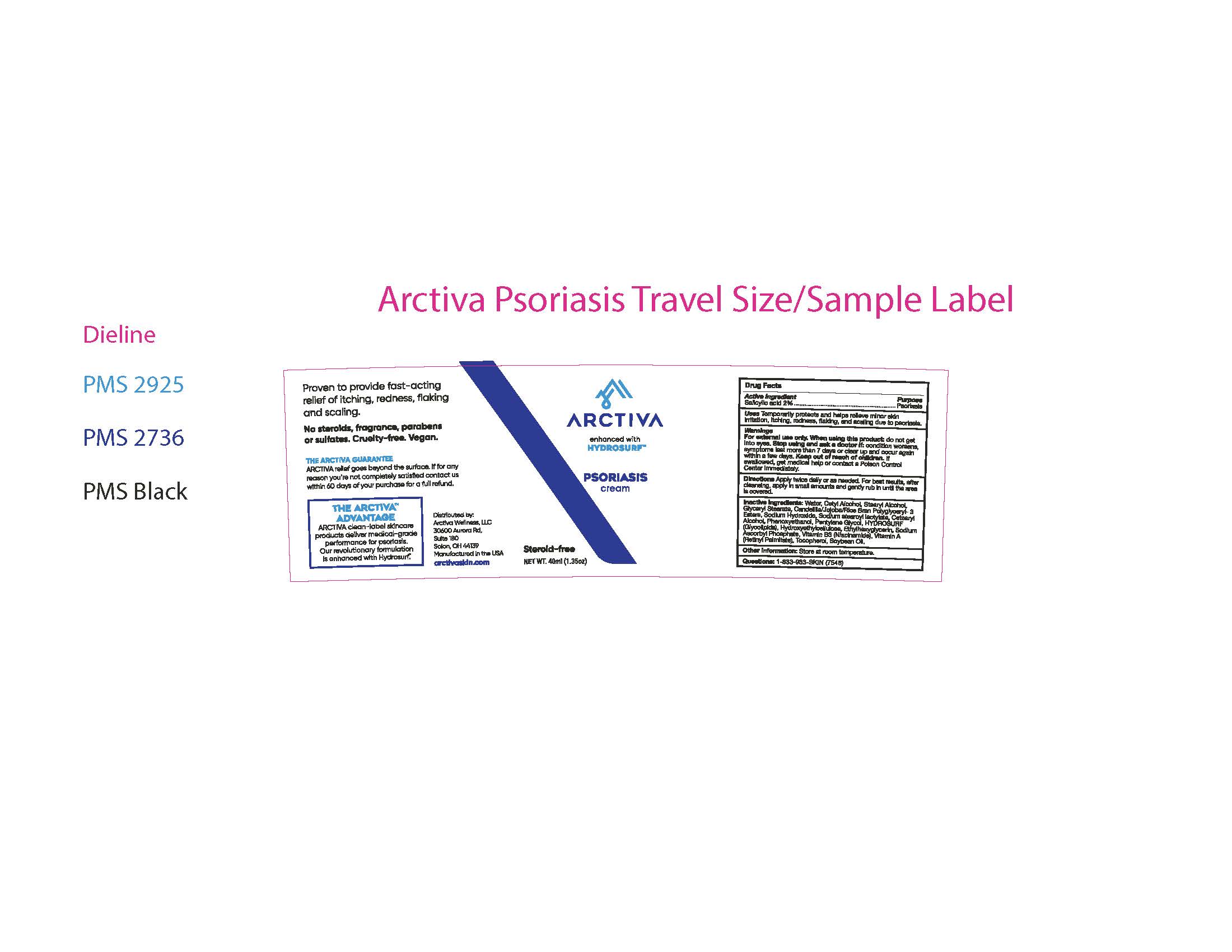 DRUG LABEL: Arctiva Psoriasis Cream
NDC: 58418-822 | Form: CREAM
Manufacturer: Epic Laboratories, LLC
Category: otc | Type: HUMAN OTC DRUG LABEL
Date: 20250127

ACTIVE INGREDIENTS: SALICYLIC ACID 2.6 g/130 mL
INACTIVE INGREDIENTS: SODIUM STEAROYL LACTYLATE; NIACINAMIDE; VITAMIN A PALMITATE; CANDELILLA WAX; GLYCERYL MONOSTEARATE; CETOSTEARYL ALCOHOL; STEARYL ALCOHOL; RICE BRAN; LIPID A 504; SODIUM ASCORBYL PHOSPHATE; SODIUM HYDROXIDE; HYDROXYETHYL CELLULOSE (280 MPA.S AT 2%); POLYGLYCERIN-3; JOJOBA OIL, RANDOMIZED; WATER; CETYL ALCOHOL; PENTYLENE GLYCOL; PHENOXYETHANOL; ETHYLHEXYLGLYCERIN

Arctiva Psoriasis Cream

Active Ingredient
Salysilic Acid 2%.........

Purpose.... Psoriasis

INDICATIONS AND USAGE

Uses: Temporarily protects and helps relieve minor skin irritation and itching due to psoriasis.

Warnings

For external use only. When using this product: do not get into eyes.

Stop using and ask a doctor if: condition worsen, symptoms last more than

7 days or clear up and occur again within a few days.

Keep out of reach of children. If swallowed, get medical help or contact a

Poison Control Center immediately.

DOSAGE AND ADMINISTRATION

Directions Apply twice daily or as needed.

For best results apply after cleansing.

Inactive Ingredients: Water, Cetyl Alcohol,

Stearyl Alcohol, Glyceryl Stearate,

Candelilla/Jojoba/Rice Bran Polyglyceryl- 3

Esters, Sodium Hydroxide, Sodium stearoyl

lactylate, Cetearyl Alcohol, Phenoxyethanol,

Pentylene Glycol, Hydrosurf (Glycolipids),

Hydroxyethylcellulose, Ethylhexyglycerin,

Sodium Ascorbyl Phosphate, Vitamin B3

(Niacinamide), Vitamin A (Retinyl Palmitate),

Tocopherol, Soybean Oil.

Other Information: Store at room temperature.

Questions: 1-833-933-SKIN (7546)

THE ARCTIVA GUARANTEE

Arctiva relief goes beyond the surface. If for any reason

you're not completely satisfied contact us within 60days of your purchase for a

full refund.

Distributed by:

Arctiva Wellness, LLC

30600 Aurora Rd.

Suite 180

Solon, OH 44139

Made in U.S.A

arctivaskin.com